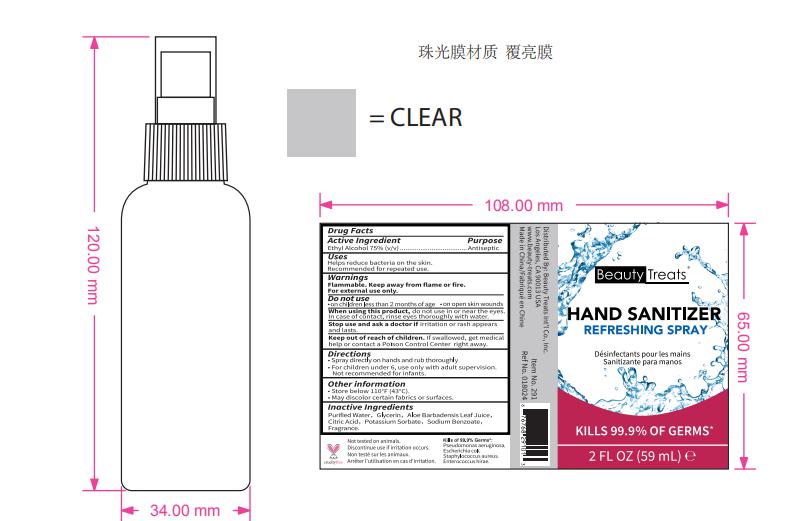 DRUG LABEL: BeautyTreats HAND SANITIZER
NDC: 74765-015 | Form: SPRAY
Manufacturer: Zhejiang Yiwu Limei Cosmetics Co., Ltd
Category: otc | Type: HUMAN OTC DRUG LABEL
Date: 20200531

ACTIVE INGREDIENTS: ALCOHOL 75 mL/100 mL
INACTIVE INGREDIENTS: FRAGRANCE LAVENDER & CHIA F-153480; WATER

NA

Active Ingredient(s)

Ethyl Alcohol 75% v/v. Purpose: Antiseptic

Purpose

Antiseptic, Hand Sanitizer

Use

Helps reduce bacteria on the skin, Recommended repeated use..

Warnings

Flammable. Keep away from flame or fire, For external use only.

Do not use

- in children less than 2 months of age
- on open skin wounds

When using this product do not use in or near the eyes. In case of contact, rinse eyes thoroughly with water.
Stop use and ask a doctor if irritation or rash appears and lasts.
Keep out of reach of children. If swallowed, get medical help or contact a Poison Control Center right away.

Stop use and ask a doctor if irritation or rash appears and lasts.

Keep out of reach of children. If swallowed, get medical help or contact a Poison Control Center right away.

Directions

- spray directly on hands and rub thoroughly
- for children under 6 , use only with adult supervision. Not recommended for infants.

Other information

- Store below 110F (43F)
- May discolor certain fabrics or surfaces

Inactive ingredients

purified water, Fragrance

Package Label - Principal Display Panel

59 mL NDC: 74765-015-01